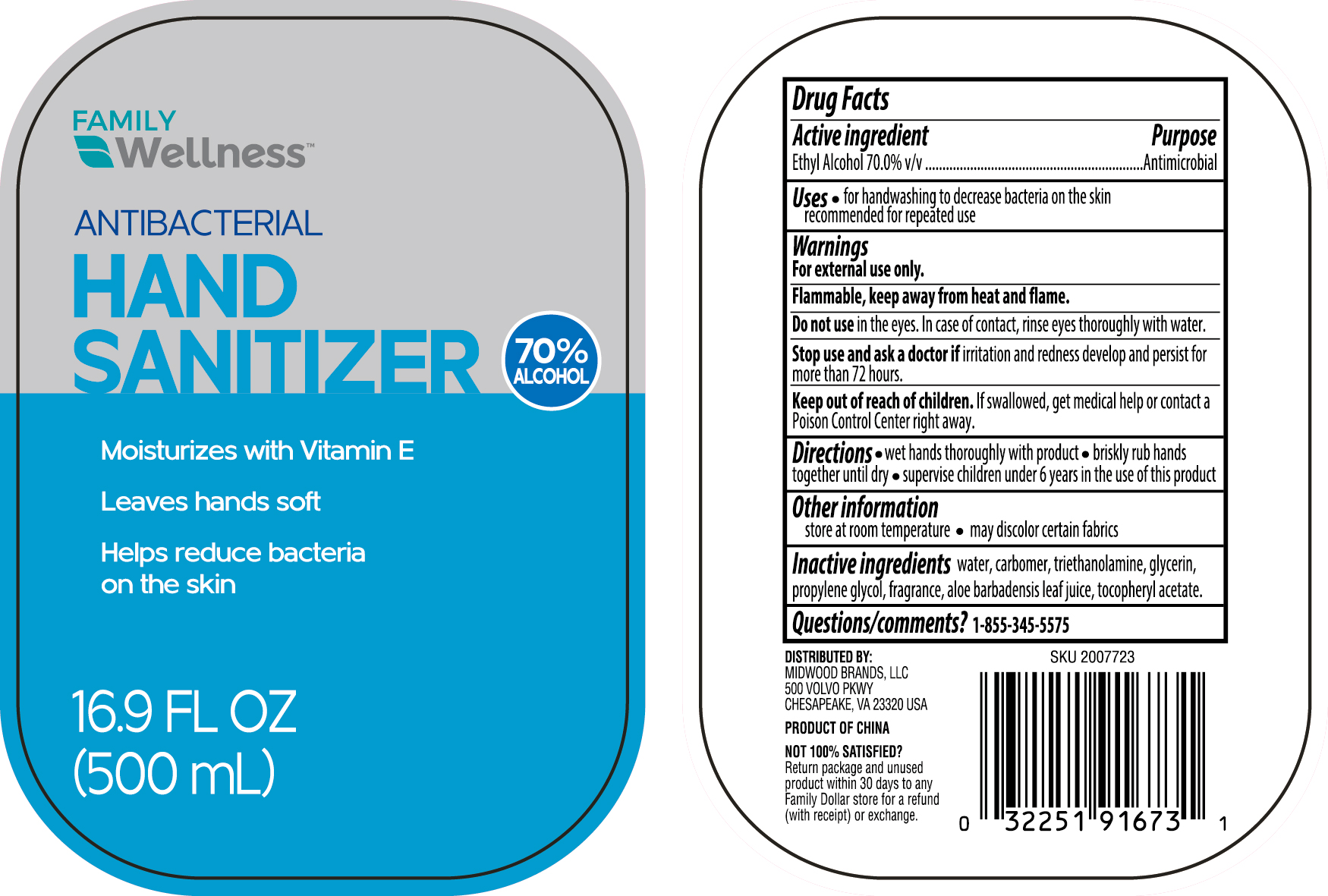 DRUG LABEL: Hand sanitizer 16.9oz with vitamin E
NDC: 75742-029 | Form: LIQUID
Manufacturer: Zhejiang Guoyao Jingyue Aerosol Co., Ltd.
Category: otc | Type: HUMAN OTC DRUG LABEL
Date: 20260105

ACTIVE INGREDIENTS: ALCOHOL 70 mL/100 mL
INACTIVE INGREDIENTS: WATER; CARBOMER HOMOPOLYMER, UNSPECIFIED TYPE; ALOE VERA LEAF; PROPYLENE GLYCOL; GLYCERIN; TROLAMINE; .ALPHA.-TOCOPHEROL ACETATE

Hand sanitizer 16.9oz with vitamin E

Active ingredient

Ethyl Alcohol 70.0%v/v

Purpose

Antimicrobial

Uses

For hand washing to decrease bacteria on the skin

Recommended for repeated use

Warnings

For external use only

Flammable, keep away from heat and flame.

Do not use in the eyes. In case of contact, rinse eyes thoroughly with water.

Stop use and ask a doctor if irritation and redness develop and persist for more than 72 hours.

Keep out of reach of children.

If swallowed, get medical help or contact a Poison Control Center right away.

Directions

wet hands thoroughly with product

Briskly rub hands together until dry

Supervise children under 6 years in the use of this product

Other information

Store at room temperature

May discolor certain fabrics

Inactive ingredients

water, carbomer, triethanolamine, glycerin, propylene glycol, fragrance, aloe barbadensis leaf juice, tocopheryl acetate